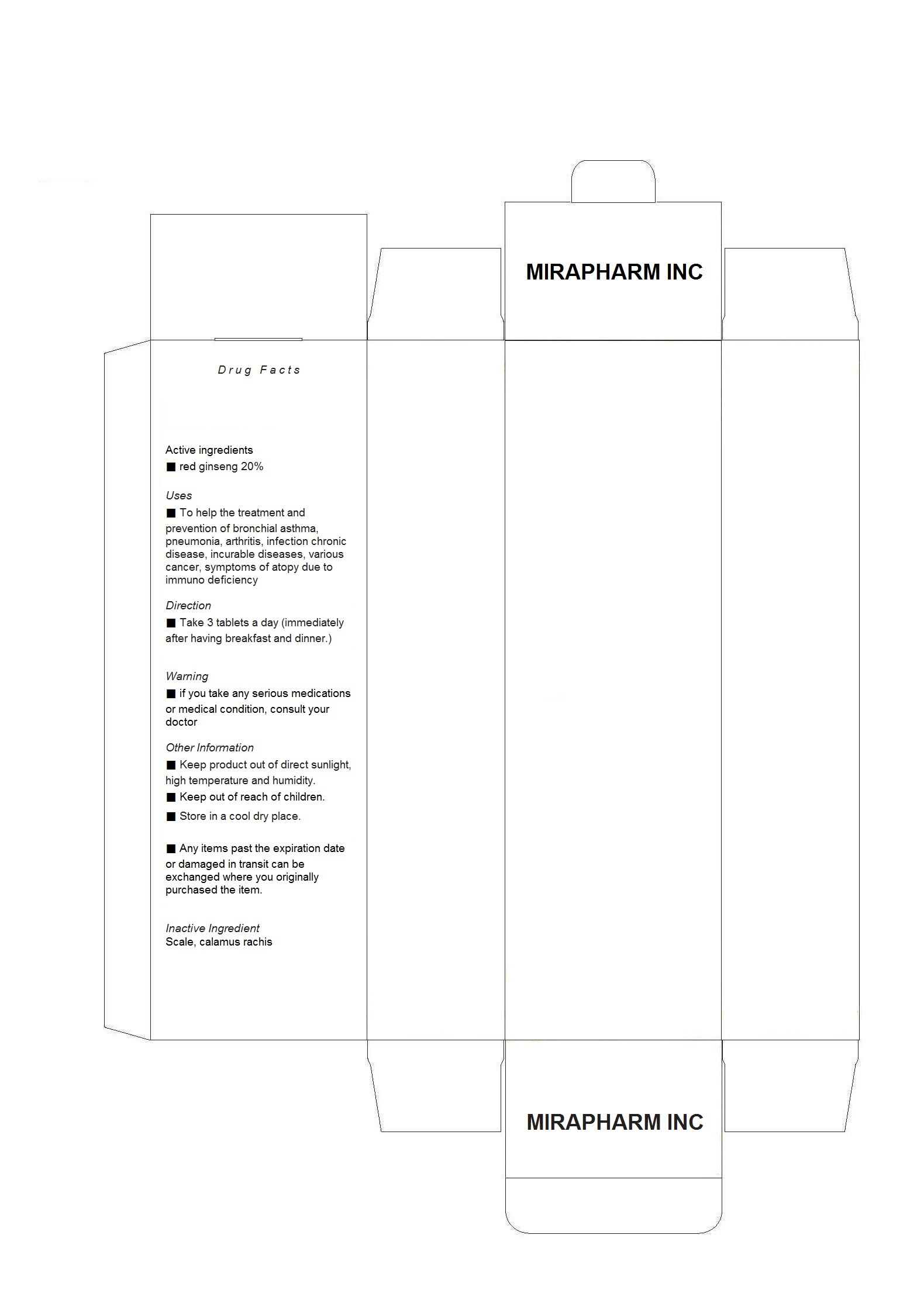 DRUG LABEL: SUPER MEDIPHARM
NDC: 61065-1003 | Form: CAPSULE
Manufacturer: Mirapharm Inc
Category: otc | Type: HUMAN OTC DRUG LABEL
Date: 20170206

ACTIVE INGREDIENTS: PANAX GINSENG WHOLE 0.3 g/1 1
INACTIVE INGREDIENTS: CALAMUS OIL

Drug Facts

ACTIVE INGREDIENT

red ginseng

INACTIVE INGREDIENT

scale calamus, rachis

PURPOSE

to help the treatment and prevention of bronchial asthma, pneumonia, arthritis, infection chronic disease, incurable diseases, various cancer, symptoms of atopy due to immuno deficiency

keep out or reach of the children

INDICATIONS AND USAGE

take 3 tablets a day (immediately after having breakfast and dinner)

WARNINGS

if you take any serious medications or medical condition, consult your doctor

DOSAGE AND ADMINISTRATION

for oral use only